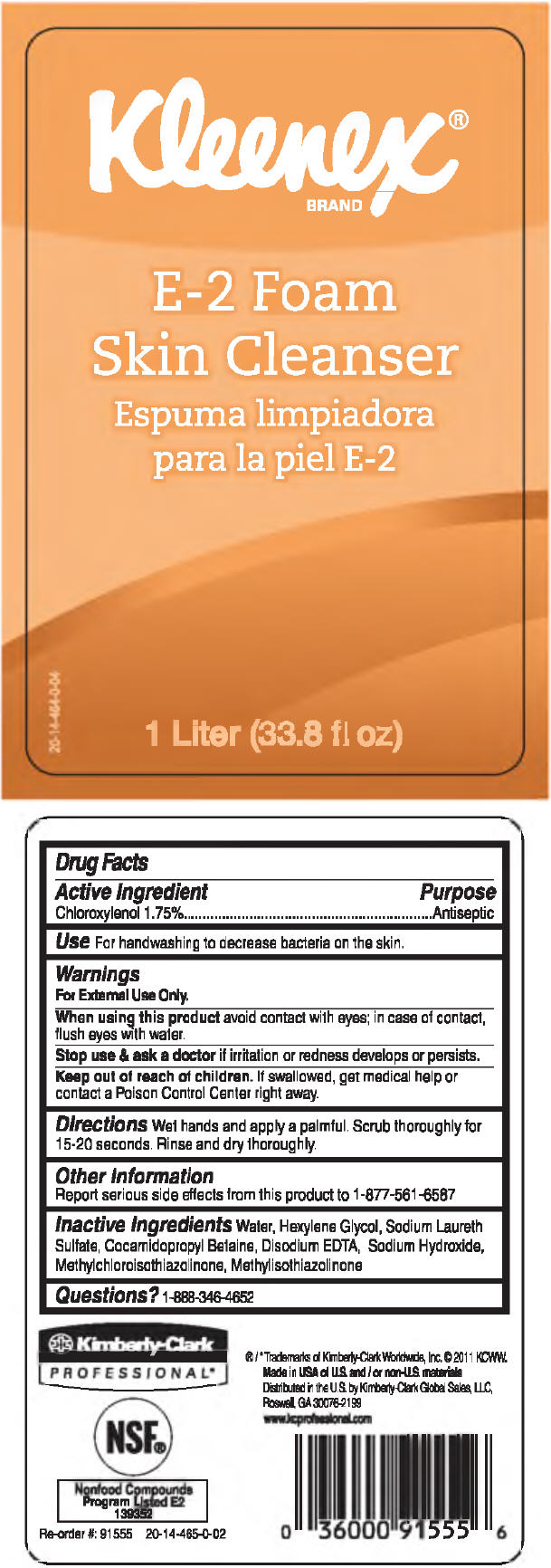 DRUG LABEL: KLEENEX E2 Foam Skin Cleanser
NDC: 55118-570 | Form: SOLUTION
Manufacturer: Kimberly-Clark Corporation
Category: otc | Type: HUMAN OTC DRUG LABEL
Date: 20120510

ACTIVE INGREDIENTS: Chloroxylenol 0.0175 L/1 L
INACTIVE INGREDIENTS: Water; Hexylene Glycol; Sodium Laureth Sulfate; Cocamidopropyl Betaine; Edetate Disodium; Sodium Hydroxide; Methylchloroisothiazolinone; Methylisothiazolinone

KLEENEX® E2 Foam Skin Cleanser

Drug Facts

Active Ingredient

Chloroxylenol 1.75%

Purpose

Antiseptic

Use

For handwashing to decrease bacteria on the skin.

Warnings

For External Use Only.

When using this product avoid contact with eyes; in case of contact, flush eyes with water.

Stop use & ask a doctor if irritation or redness develops or persists.

Keep out of reach of children. If swallowed, get medical help or contact a Poison Control Center right away.

Directions

Wet hands and apply a palmful. Scrub thoroughly for 15-20 seconds. Rinse and dry thoroughly.

Other Information

Report serious side effects from this product to 1-877-561 -6587

Inactive Ingredients

Water, Hexylene Glycol, Sodium Laureth Sulfate, Cocamidopropyl Betaine, Disodium EDTA, Sodium Hydroxide, MethylchloroisothiazoIinone, Methylisothiazolinone

Questions ?

1-888-346-4652

Distributed in the U.S. by Kimberly-Clark Global Sales, LLC,
Roswell, GA 30076-2199

PRINCIPAL DISPLAY PANEL - 1 Liter Container Label

Kleenex®
BRAND

E-2 Foam
Skin Cleanser

1 Liter (33.8 fl oz)

20-14-464-0-04